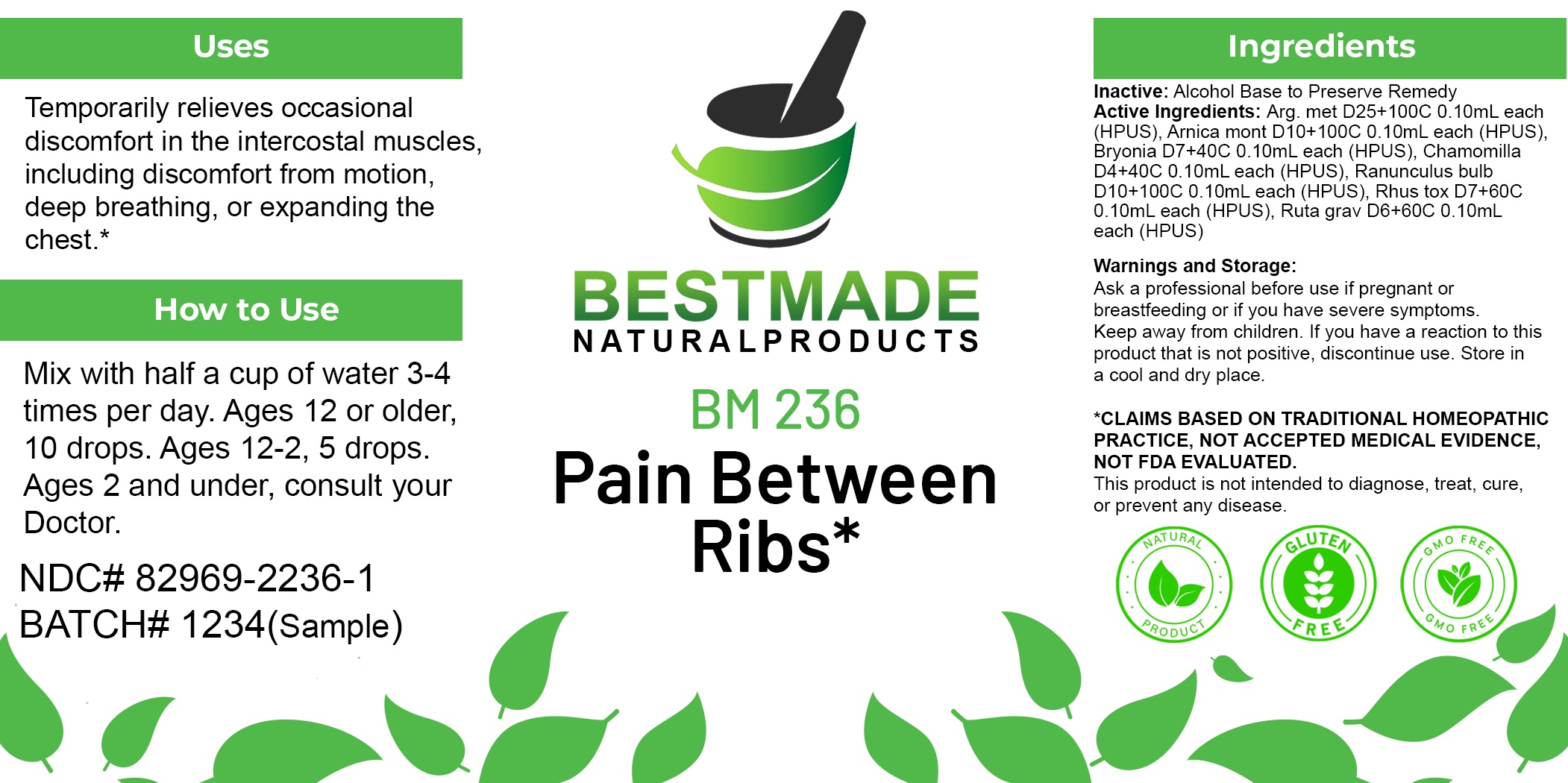 DRUG LABEL: Bestmade Natural Products BM236
NDC: 82969-2236 | Form: LIQUID
Manufacturer: Bestmade Natural Products
Category: homeopathic | Type: HUMAN OTC DRUG LABEL
Date: 20250304

ACTIVE INGREDIENTS: SILVER NITRATE 30 [hp_C]/30 [hp_C]; ARNICA MONTANA 30 [hp_C]/30 [hp_C]; RANUNCULUS BULBOSUS 30 [hp_C]/30 [hp_C]; BRYONIA ALBA ROOT 30 [hp_C]/30 [hp_C]; TOXICODENDRON PUBESCENS LEAF 30 [hp_C]/30 [hp_C]; MATRICARIA CHAMOMILLA 30 [hp_C]/30 [hp_C]; RUTA GRAVEOLENS FLOWERING TOP 30 [hp_C]/30 [hp_C]
INACTIVE INGREDIENTS: ALCOHOL 30 [hp_C]/30 [hp_C]

BM236

DOSAGE AND ADMINISTRATION

How to Use

Mix with half a cup of water 3-4 times per day. Ages 12 or older, 10 drops. Ages 12-2, 5 drops. Ages 2 and under, consult your Doctor.

Inactive:

Alcohol Base to Preserve Product

ACTIVE INGREDIENT

Active Ingredients: Arg. met D25+100C 0.10mL each (HPUS), Arnica mont D10+100C 0.10mL each (HPUS), Bryonia D7+40C 0.10mL each (HPUS), Chamomilla D4+40C 0.10mL each (HPUS), Ranunculus bulb D10+100C 0.10mL each (HPUS), Rhus tox D7+60C 0.10mL each (HPUS), Ruta grav D6+60C 0.10mL each (HPUS)

KEEP OUT OF REACH OF CHILDREN

Warnings and Storage:

Ask a professional before use if pregnant or breastfeeding or if you have severe symptoms.

Keep away from children. If you have a reaction to this product that is not positive, discontinue use. Store in a cool and dry place

*CLAIMS BASED ON TRADITIONAL HOMEOPATHIC PRACTICE, NOT ACCEPTED MEDICAL EVIDENCE NOT FDA EVALUATED.
This product is not intended to diagnose, treat, cure, or prevent any disease.

Warnings and Storage:

Ask a professional before use if pregnant or breastfeeding or if you have severe symptoms.

Keep away from children. If you have a reaction to this product that is not positive, discontinue use. Store in a cool and dry place

*CLAIMS BASED ON TRADITIONAL HOMEOPATHIC PRACTICE, NOT ACCEPTED MEDICAL EVIDENCE NOT FDA EVALUATED.
This product is not intended to diagnose, treat, cure, or prevent any disease.

Uses
Temporarily relieves occasional discomfort in the intercostal muscles, including discomfort from motion, deep breathing, or expanding the chest.*

Uses
Temporarily relieves occasional discomfort in the intercostal muscles, including discomfort from motion, deep breathing, or expanding the chest.*

Entire package label